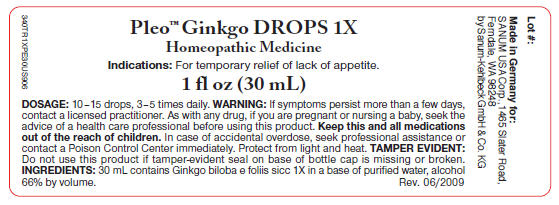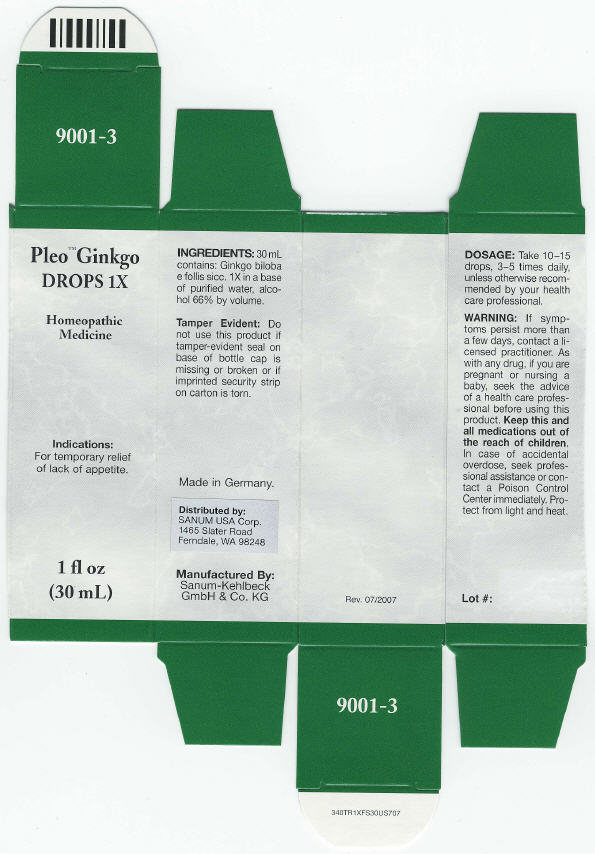 DRUG LABEL: Pleo Ginkgo
NDC: 60681-9001 | Form: SOLUTION/ DROPS
Manufacturer: Sanum-Kehlbeck GmbH & Co. KG
Category: homeopathic | Type: HUMAN OTC DRUG LABEL
Date: 20090918

ACTIVE INGREDIENTS: ginkgo biloba leaf 1 [HP_X]/30 mL
INACTIVE INGREDIENTS: water

Pleo™ Ginkgo
DROPS 1X

Homeopathic Medicine

Indications

For temporary relief of lack of appetite.

INGREDIENTS

30 mL contains: Ginkgo biloba e follis sicc. 1X in a base of purified water, alcohol 66% by volume.

Tamper Evident

Do not use this product if tamper-evident seal on base of bottle cap is missing or broken or if imprinted security strip on carton is torn.

DOSAGE

Take 10–15 drops, 3–5 times daily, unless otherwise recommended by your health care professional.

WARNING

If symptoms persist more than a few days, contact a licensed practitioner. As with any drug, if you are pregnant or nursing a baby, seek the advice of a health care professional before using this product.

KEEP OUT OF REACH OF CHILDREN

Keep this and all medications out of the reach of children. In case of accidental overdose, seek professional assistance or contact a Poison Control Center immediately.

STORAGE AND HANDLING

Protect from light and heat.

Made in Germany.

Distributed by:
SANUM USA Corp.
1465 Slater Road
Ferndale, WA 98248

Manufactured By:
Sanum-Kehlbeck
GmbH & Co. KG

Rev. 07/2007

PRINCIPAL DISPLAY PANEL - 30 mL Label

Pleo™ Ginkgo DROPS 1X

Homeopathic Medicine

Indications: For temporary relief of lack of appetite.

1 fl oz (30 mL)

DOSAGE: 10–15 drops, 3–5 times daily. WARNING: If symptoms persist more than a few days,
contact a licensed practitioner. As with any drug, if you are pregnant or nursing a baby, seek the
advice of a health care professional before using this product. Keep this and all medications
out of the reach of children. In case of accidental overdose, seek professional assistance or
contact a Poison Control Center immediately. Protect from light and heat. TAMPER EVIDENT:
Do not use this product if tamper-evident seal on base of bottle cap is missing or broken.
INGREDIENTS: 30 mL contains Ginkgo biloba e foliis sicc 1X in a base of purified water, alcohol
66% by volume.
Rev. 06/2009

PRINCIPAL DISPLAY PANEL - 30 mL box

Pleo™ Ginkgo
DROPS 1X

Homeopathic
Medicine

lndications:
For
temporary relief
of lack of appetite.

1 fl oz
(30 mL)